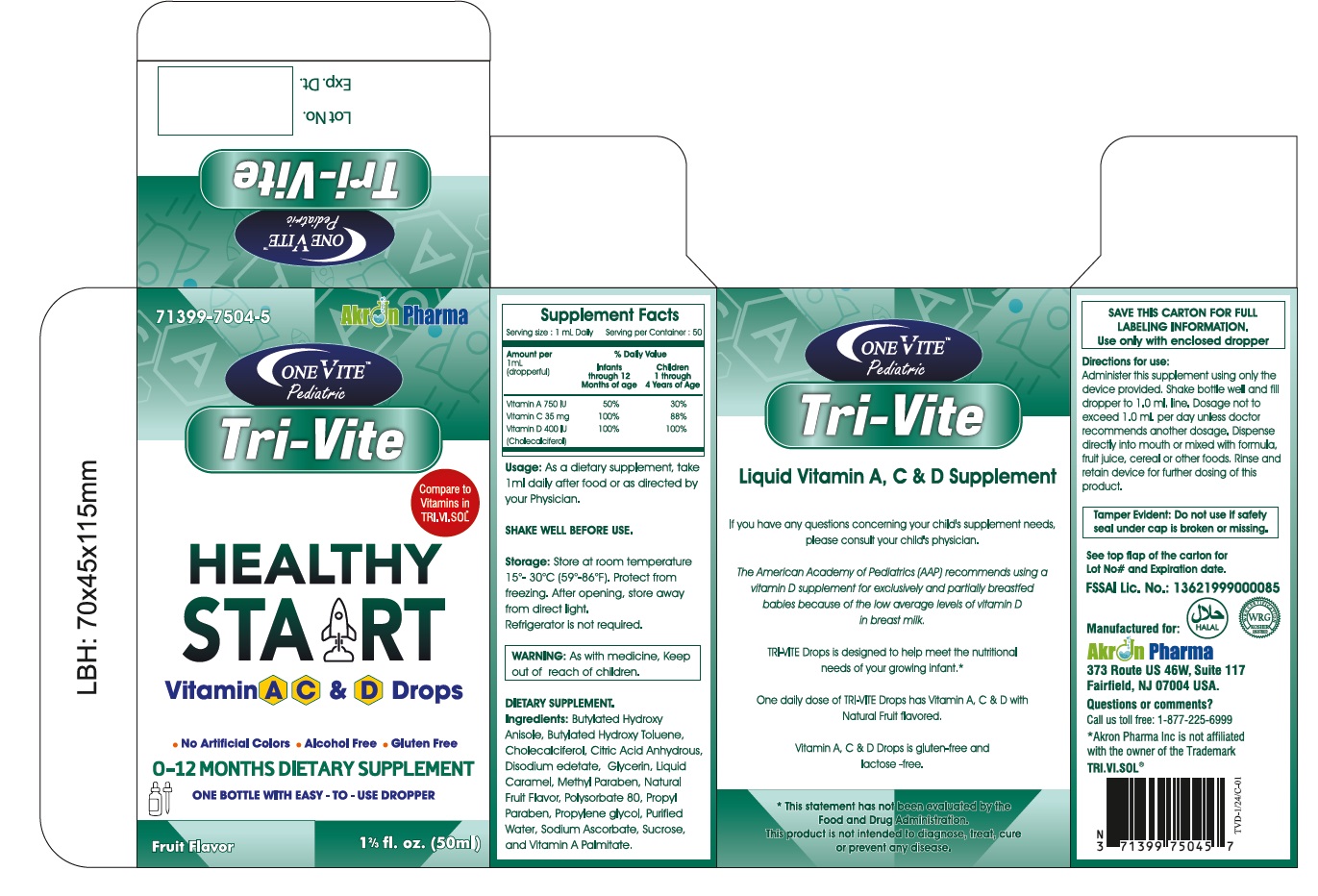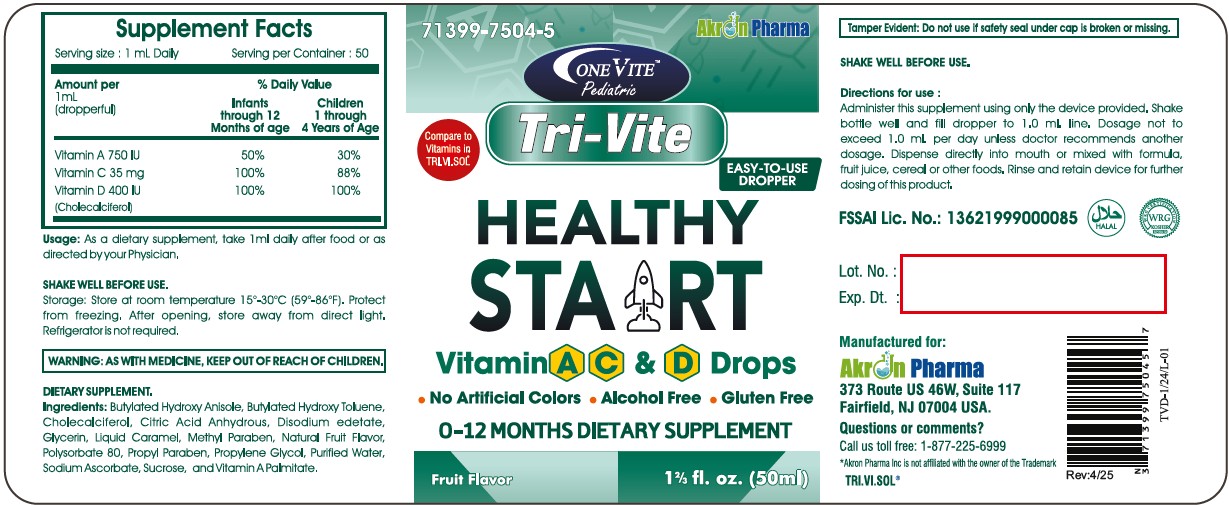 DRUG LABEL: Tri-Vite Pediatric Oral Solution
NDC: 71399-7504 | Form: SOLUTION
Manufacturer: Akron Pharma Inc.
Category: other | Type: DIETARY SUPPLEMENT
Date: 20250505

ACTIVE INGREDIENTS: VITAMIN A PALMITATE .225 mg/1 mL; SODIUM ASCORBATE 35 mg/1 mL; CHOLECALCIFEROL .01 mg/1 mL
INACTIVE INGREDIENTS: SUCROSE; GLYCERIN; PROPYLENE GLYCOL; POLYSORBATE 80; METHYLPARABEN; ANHYDROUS CITRIC ACID; EDETATE DISODIUM; PROPYLPARABEN; CARAMEL; BUTYLATED HYDROXYANISOLE; BUTYLATED HYDROXYTOLUENE; WATER

OneVite Pediatric
TRI-VITE Drops
Vitamin A C and D
Healthy Start

STATEMENT OF IDENTITY

Supplement Facts

Serving size: 1 mL Daily

Serving per container: 50

Amount per 1mL (dropperful) % Daily Value

Infants through 12 Months of age Children 1 through 4 Years of age

Vitamin A 225 mcg 50% 30%

Vitamin C 35 mg 100% 88%

Vitamin D 10 mcg 100% 100%

HEALTH CLAIM

TRI-VITE Drops is designed to help meet the nutritional needs of your growing infant.*

* This statement has not been evaluated by the Food and Drug Administration. This product is not intended to diagnose, treat, cure or prevent any disease.

SAFE HANDLING WARNING

Storage: Store at room temperature 15º-30ºC(59º-86ºF). Protect from freezing. After opening, store away from direct light. Refrigerator is not required.

WARNINGS

WARNING: As with medicine, Keep out of reach of children.

PRECAUTIONS

SHAKE WELL BEFORE USE.

DOSAGE AND ADMINISTRATION

Directions for use:

Administer this supplement using only the device provided. Shake bottle well and fill dropper to 1.0 ml. line. Dosage not to exceed 1.0 ml. per day unless doctor recommends another dosage. Dispense directly into mouth or mixed with formula, fruit juice, cereal or other foods. Rinse and retain device for further dosing of this product.